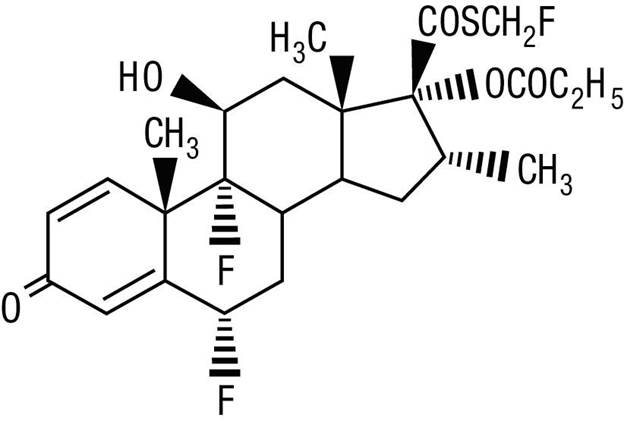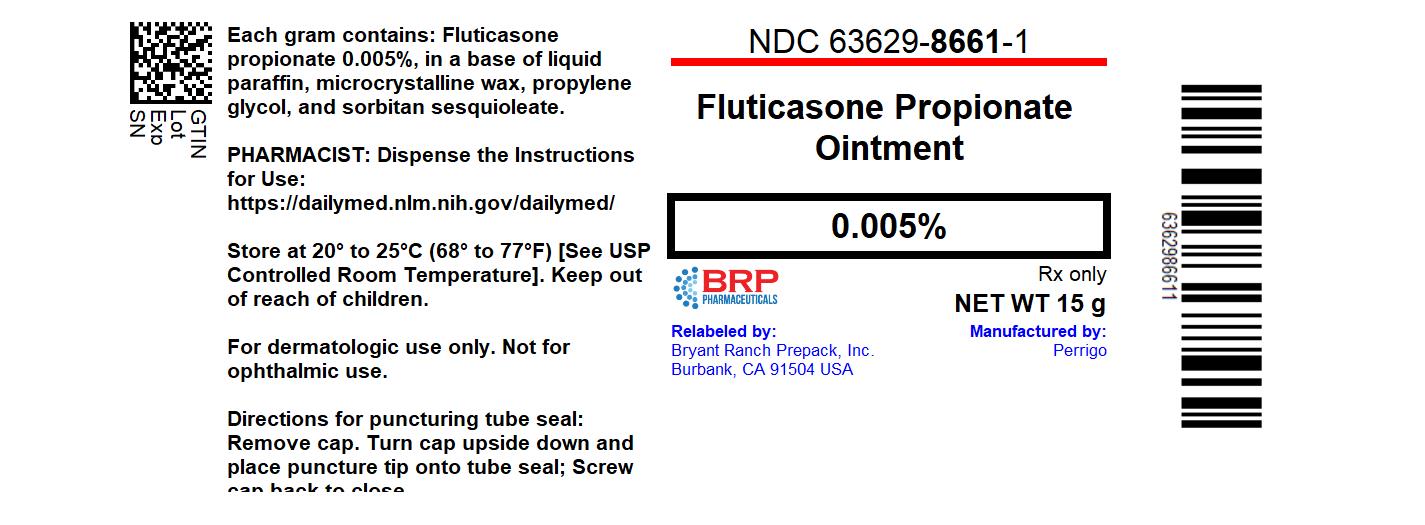 DRUG LABEL: Fluticasone Propionate
NDC: 63629-8661 | Form: OINTMENT
Manufacturer: Bryant Ranch Prepack
Category: prescription | Type: HUMAN PRESCRIPTION DRUG LABEL
Date: 20240404

ACTIVE INGREDIENTS: FLUTICASONE PROPIONATE 0.05 mg/1 g
INACTIVE INGREDIENTS: MICROCRYSTALLINE WAX; PROPYLENE GLYCOL; SORBITAN SESQUIOLEATE; MINERAL OIL

HIGHLIGHTS OF PRESCRIBING INFORMATION

These highlights do not include all the information needed to use FLUTICASONE PROPIONATE OINTMENT safely and effectively. See full prescribing information for FLUTICASONE PROPIONATE OINTMENT.
FLUTICASONE PROPIONATE ointment, for topical use
Initial U.S. Approval: 1990

RECENT MAJOR CHANGES

Warnings and Precautions, Ophthalmic Adverse Reaction (5.5) 03/2021

1 INDICATIONS AND USAGE

Fluticasone propionate ointment is a corticosteroid indicated for the relief of the inflammatory and pruritic manifestations of corticosteroid-responsive dermatoses in adult patients. (1)

2 DOSAGE AND ADMINISTRATION

Apply a thin film to affected skin areas twice daily. (2)

Not for ophthalmic, oral or intravaginal use. (2)

3 DOSAGE FORMS AND STRENGTHS

Ointment, 0.005%. (3)

4 CONTRAINDICATIONS

History of serious hypersensitivity to fluticasone propionate, or any other components of fluticasone propionate ointment. (4)

5 WARNINGS AND PRECAUTIONS

- Hypothalamic-Pituitary-Adrenal (HPA) Axis Suppression: Reversible HPA axis suppression and resulting clinical glucocorticoid insufficiency can occur during or after withdrawal of treatment. Risk factors include use over large surface area, prolonged use, use under occlusion, altered skin barrier, liver failure, and young age. Modify use if HPA axis suppression is suspected. (5.1)
- Local adverse reactions with topical corticosteroids may occur more frequently with the use of occlusive dressings, prolonged use, or use of higher potency corticosteroids. These reactions include: irritation, dryness, acneiform eruptions, hypertrichosis, hypopigmentation, perioral dermatitis, allergic contact dermatitis, secondary infection, striae and miliaria. (5.2)
- Ophthalmic Adverse Reactions: May increase the risk of cataract and glaucoma. If visual symptoms occur, consider referral to an ophthalmologist. (5.5)

6 ADVERSE REACTIONS

The most common adverse reactions (<1%) were pruritus, burning, hypertrichosis, increased erythema, urticaria, irritation, and lightheadedness. (6.1)

To report SUSPECTED ADVERSE REACTIONS, contact Padagis® at 1-866-634-9120 or FDA at 1-800-FDA-1088 or www.fda.gov/medwatch.

FULL PRESCRIBING INFORMATION

1 INDICATIONS AND USAGE

Fluticasone propionate ointment is a corticosteroid indicated for the relief of the inflammatory and pruritic manifestations of corticosteroid-responsive dermatoses in adult patients.

2 DOSAGE AND ADMINISTRATION

Apply a thin film of fluticasone propionate ointment to the affected skin areas twice daily. Rub in gently.

Avoid use with occlusive dressing.

Fluticasone propionate ointment is for topical use only; it is not for ophthalmic, oral, or intravaginal use.

3 DOSAGE FORMS AND STRENGTHS

Ointment, 0.005%. Each gram of fluticasone propionate ointment contains 0.05 mg fluticasone propionate in a white to off-white translucent ointment base.

4 CONTRAINDICATIONS

Fluticasone propionate ointment is contraindicated in patients with a history of hypersensitivity to any of the components in the preparation.

5 WARNINGS AND PRECAUTIONS

5.1 Hypothalamic-Pituitary-Adrenal (HPA) Axis Suppression and Other Adverse Endocrine Effects

Topical corticosteroids, including fluticasone propionate ointment, can produce reversible HPA axis suppression with the potential for clinical glucocorticoid insufficiency. Factors that predispose to HPA axis suppression include large treatment surface areas, prolonged use, use under occlusion, altered skin barrier, liver failure, and young age. Cushing’s syndrome, hyperglycemia, and unmasking of latent diabetes mellitus can also result from systemic absorption of topical corticosteroids.

HPA axis suppression may occur during or after withdrawal of treatment. If HPA axis suppression is suspected, gradually withdraw the drug, reduce the frequency of application, or substitute with a less potent corticosteroid. Evaluation of HPA axis suppression may be done by using the cosyntropin stimulation test.

Pediatric patients may be at greater risk of HPA axis suppression due to their higher skin surface area to body mass ratios [see Use in Specific Populations (8.4)].

5.2 Local Adverse Reactions

The following local adverse reactions have been reported with topical corticosteroids. They may occur more frequently with the use of occlusive dressings and higher potency corticosteroids. These reactions are listed in an approximate decreasing order of occurrence: irritation, folliculitis, acneiform eruptions, hypopigmentation, perioral dermatitis, allergic contact dermatitis, secondary infection, skin atrophy, striae, hypertrichosis, and miliaria.

5.3 Allergic Contact Dermatitis

Allergic contact dermatitis with topical corticosteroids is usually diagnosed by observing failure to heal rather than noting a clinical exacerbation. Such an observation can be corroborated with appropriate diagnostic patch testing. Discontinue fluticasone propionate ointment if appropriate.

5.4 Skin Infections

If concomitant skin infections are present or develop, use an appropriate antimicrobial. If a favorable response does not occur promptly, discontinue use of fluticasone propionate ointment until the infection has been adequately controlled.

5.5 Ophthalmic Adverse Reactions

Use of topical corticosteroids may increase the risk of posterior subcapsular cataracts and glaucoma. Cataracts and glaucoma have been reported postmarketing with the use of topical corticosteroids.

Avoid contact of fluticasone propionate ointment with eyes. Advise patients to report any visual symptoms and consider referral to an ophthalmologist for evaluation.

6 ADVERSE REACTIONS

The following adverse reactions are discussed in greater detail in other sections of the labeling:

- HPA Axis Suppression and Other Adverse Endocrine Effects [see Warnings and Precautions (5.1)]
- Local Adverse Reactions [see Warnings and Precautions (5.2)]
- Concomitant Skin Infections [see Warnings and Precautions (5.4)]

6.1 Clinical Trials Experience

Because clinical trials are conducted under widely varying conditions, adverse reaction rates observed in the clinical trials of a drug cannot be directly compared to rates in the clinical trials of another drug and may not reflect the rates observed in practice.

In controlled clinical trials, the total incidence of adverse reactions associated with the use of fluticasone propionate ointment was approximately 4%. These adverse reactions were usually mild, self-limiting, and consisted primarily of pruritus, burning, hypertrichosis, increased erythema, urticaria, irritation, and lightheadedness. Each of these events occurred individually in less than 1% of subjects.

6.2 Postmarketing Experience

Because these reactions are reported voluntarily from a population of uncertain size, it is not always possible to reliably estimate their frequency or establish a causal relationship to drug exposure.

The following local adverse reactions have been identified during post-approval use of fluticasone propionate ointment: acneiform dermatitis, edema, rash, hypoaesthesia, pustular psoriasis, skin atrophy.

The following systemic adverse reactions have been identified during post-approval use of fluticasone propionate ointment: immunosuppression/Pneumocystis jirovecii/pneumonia/leukopenia/thrombocytopenia; hyperglycemia/glycosuria; Cushing syndrome; generalized body edema/blurred vision; and acute urticarial reaction (edema, urticaria, pruritus, and throat swelling).

The following local adverse reactions have also been reported with the use of topical corticosteroids: telangiectasia, striae, dryness, folliculitis, hypopigmentation, perioral dermatitis, allergic contact dermatitis, secondary infection, and miliaria.

Ophthalmic adverse reactions including cataracts, glaucoma and increased intraocular pressure have been reported with the use of topical corticosteroids.

8 USE IN SPECIFIC POPULATIONS

8.1 Pregnancy

Risk Summary

There are no available data on fluticasone propionate ointment use in pregnant women to evaluate for a drug-associated risk of major birth defects, miscarriage, or adverse maternal or fetal outcomes. Observational studies suggest an increased risk of low birthweight infants with the use of greater than 300 grams of potent or very potent topical corticosteroids during pregnancy (see Data). Advise pregnant women that fluticasone propionate ointment may increase the risk of having a low birthweight infant and to use fluticasone propionate ointment on the smallest area of skin and for the shortest duration possible.

In animal reproduction studies, subcutaneous administration of fluticasone propionate to pregnant mice, rats, and rabbits during organogenesis caused malformations characteristic of corticosteroids in each species (see Data). The available data do not allow the calculation of relevant comparisons between the systemic exposure of fluticasone propionate observed in animal studies to the systemic exposure that would be expected in humans after topical use of fluticasone propionate ointment.

The background risk of major birth defects and miscarriage for the indicated population(s) is unknown. All pregnancies have a background risk of birth defect, loss, or other adverse outcomes. In the U.S. general population, the estimated background risk of major birth defects and miscarriage in clinically recognized pregnancies is 2 to 4% and 15 to 20%, respectively.

Data

Human Data

Available observational studies in pregnant women did not identify a drug-associated risk of major birth defects, preterm delivery, or fetal mortality with the use of topical corticosteroids of any potency. However, when the dispensed amount of potent or very potent topical corticosteroids exceeded 300 grams during the entire pregnancy, maternal use was associated with an increased risk of low birth weight infants.

Animal Data

In embryo-fetal development studies, pregnant rabbits, rats, and mice received subcutaneous doses of fluticasone propionate during organogenesis at doses up to 4, 100, and 150 μg/kg/day, respectively. A malformation characteristic of corticosteroids (cleft palate) was noted at the high dose in each species. Additional adverse effects were noted in rats and rabbits. Decreased fetal weights and retarded skeletal ossification were noted in rabbits at 4 μg/kg/day and rats at 100 μg/kg/day. Maternal toxicity and omphalocele were also noted in rats at 100 μg/kg/day. No malformations or developmental toxicity was noted in rabbits at 0.57 μg/kg/day, in rats at 10 μg/kg/day, or in mice at 15 μg/kg/day. Fluticasone propionate crossed the placenta following administration of a subcutaneous or an oral dose of 100 μg/kg tritiated fluticasone propionate to pregnant rats.

8.2 Lactation

Risk Summary

There are no data on the presence of fluticasone propionate in human milk, its effects on the breastfed infant, or its effects on milk production. It is not known whether topical administration of fluticasone propionate ointment could result in sufficient systemic absorption to produce detectable quantities in human milk (see Clinical Considerations).

The developmental and health benefits of breastfeeding should be considered along with the mother's clinical need for fluticasone propionate ointment and any potential adverse effects on the breastfed child from fluticasone propionate ointment or from the underlying maternal condition.

Clinical Considerations

To minimize potential exposure to the breastfed infant via breast milk, use fluticasone propionate ointment on the smallest area of skin and for the shortest duration possible while breastfeeding. Advise breastfeeding women not to apply fluticasone propionate ointment directly to the nipple and areola prior to breastfeeding to avoid direct infant exposure [see Use in Specific Populations (8.4)].

8.4 Pediatric Use

The safety and effectiveness of fluticasone propionate ointment have not been established in pediatric patients. Use of fluticasone propionate ointment in pediatric patients is not recommended.

Because of a higher ratio of skin surface area to body mass, pediatric patients are at a greater risk than adults of systemic effects when treated with topical drugs. They are, therefore, also at greater risk of HPA axis suppression and adrenal insufficiency upon the use of topical corticosteroids [see Warnings and Precautions (5.1)].

In a trial of 35 pediatric subjects treated with fluticasone propionate ointment, 0.005% for atopic dermatitis over at least 35% of body surface area, subnormal adrenal function was observed with cosyntropin stimulation testing at the end of 3 to 4 weeks of treatment in 4 subjects who had normal testing prior to treatment. It is not known if these subjects had recovery of adrenal function because follow-up testing was not performed. The decreased responsiveness of cosyntropin testing was not correlated to age of subject, amount of fluticasone propionate ointment used, or serum levels of fluticasone propionate.

In the above trial, telangiectasia on the face was noted in one subject on the eighth day of a 4-week treatment period. Facial use was discontinued and the telangiectasia resolved.

HPA axis suppression, Cushing’s syndrome, linear growth retardation, delayed weight gain, and intracranial hypertension have been reported in pediatric patients receiving topical corticosteroids.

8.5 Geriatric Use

A limited number of patients above 65 years of age (n=203) have been treated with fluticasone propionate ointment in US and non-US clinical trials. No overall differences in safety or effectiveness were observed between these subjects and younger subjects, and other reported clinical experience has not identified differences in responses between the elderly and younger patients. However, greater sensitivity of some older individuals cannot be ruled out.

11 DESCRIPTION

Fluticasone Propionate Ointment, 0.005% contains fluticasone propionate [S-Fluoromethyl 6α, 9α-difluoro-11β-hydroxy-16α-methyl-3-oxo-17α-propionyloxyandrosta-1,4-diene-17β-carbothioate], a synthetic fluorinated corticosteroid, for topical use.

Chemically, fluticasone propionate is C25H31F3O5S. It has the following structural formula:

Fluticasone propionate has a molecular weight of 500.6. It is a white to off-white powder and is insoluble in water.

Each gram of fluticasone propionate ointment contains fluticasone propionate 0.05 mg in a white to off-white translucent ointment base of liquid paraffin, microcrystalline wax, propylene glycol, and sorbitan sesquioleate.

12 CLINICAL PHARMACOLOGY

12.1 Mechanism of Action

Corticosteroids play a role in cellular signaling, immune function, inflammation, and protein regulation; however, the precise mechanism of action of fluticasone propionate ointment in corticosteroid-responsive dermatoses is unknown.

12.2 Pharmacodynamics

Vasoconstrictor Assay

Studies performed with fluticasone propionate ointment indicate that it is in the medium range of potency as demonstrated in vasoconstrictor trials in healthy subjects when compared with other topical corticosteroids. However, similar blanching scores do not necessarily imply therapeutic equivalence.

12.3 Pharmacokinetics

Absorption

The extent of percutaneous absorption of topical corticosteroids is determined by many factors, including the vehicle and the integrity of the epidermal barrier. Occlusive dressing enhances penetration. Topical corticosteroids can be absorbed from normal intact skin. Inflammation and/or other disease processes in the skin increase percutaneous absorption.

In a study of 6 healthy subjects applying 25 g of fluticasone propionate ointment 0.005% twice daily to the trunk and legs for up to 5 days under occlusion, plasma levels of fluticasone ranged from 0.08 to 0.22 ng/mL.

Distribution

The percentage of fluticasone propionate bound to human plasma proteins averaged 91%. Fluticasone propionate is weakly and reversibly bound to erythrocytes. Fluticasone propionate is not significantly bound to human transcortin.

Metabolism

No metabolites of fluticasone propionate were detected in an in vitro study of radiolabeled fluticasone propionate incubated in human skin homogenate.

Fluticasone propionate is metabolized in the liver by cytochrome P450 3A4-mediated hydrolysis of the 5-fluoromethyl carbothioate grouping. This transformation occurs in 1 metabolic step to produce the inactive 17-β-carboxylic acid metabolite, the only known metabolite detected in man. This metabolite has approximately 2,000 times less affinity than the parent drug for the glucocorticoid receptor of human lung cytosol in vitro and negligible pharmacological activity in animal studies. Other metabolites detected in vitro using cultured human hepatoma cells have not been detected in man.

13 NONCLINICAL TOXICOLOGY

13.1 Carcinogenesis, Mutagenesis, Impairment of Fertility

In an oral (gavage) mouse carcinogenicity study, doses of 0.1, 0.3, and 1 mg/kg/day fluticasone propionate were administered to mice for 18 months. Fluticasone propionate demonstrated no tumorigenic potential at oral doses up to 1 mg/kg/day in this study.

In a dermal mouse carcinogenicity study, 0.05% fluticasone propionate ointment (40 μl) was topically administered for 1, 3 or 7 days/week for 80 weeks. Fluticasone propionate demonstrated no tumorigenic potential at dermal doses up to 6.7 μg/kg/day in this study.

Fluticasone propionate was not mutagenic or clastogenic in five in vitro genotoxicity tests (Ames assay, E. coli fluctuation test, S. cerevisiae gene conversion test, Chinese hamster ovary cell chromosome aberration assay and human lymphocyte chromosome aberration assay) and one in vivo genotoxicity test (mouse micronucleus assay).

In a fertility study, male and female rats received subcutaneous doses of fluticasone propionate at doses up to 50 μg/kg/day. No impairment of fertility or mating performance was observed.

16 HOW SUPPLIED/STORAGE AND HANDLING

Fluticasone Propionate Ointment, 0.005% is a white to off-white translucent ointment supplied as follows:

15 g tube (NDC 63629-8661-1)

Store at 20-25°C (68-77°F)

Repackaged/Relabeled by:
Bryant Ranch Prepack, Inc.
Burbank, CA 91504

17 PATIENT COUNSELING INFORMATION

Advise the patient to read the FDA-approved patient labeling (Patient Information).

Advise the patient:

- Avoid contact with the eyes.
- Do not bandage the treated skin area, or cover or wrap it to cause occlusion unless directed by the healthcare provider.
- Report any signs of local adverse reaction to their healthcare provider.
- Do not use on the face, underarms, or groin areas unless directed by the healthcare provider.
- Advise a woman to use fluticasone propionate ointment on the smallest area of skin and for the shortest duration possible while pregnant or breastfeeding. Advise breastfeeding women not to apply fluticasone propionate ointment directly to the nipple and areola to avoid direct infant exposure.

Manufactured by Padagis®
Yeruham, Israel
www.padagis.com

Rev 11-23
57B00 RC PH2

PATIENT INFORMATION

Fluticasone Propionate (floo-TIK-a-sone PROE-pee-oh-nate) Ointment, 0.005%

Important: Fluticasone propionate ointment is for use on skin only (topical).

Do not get fluticasone propionate ointment near or in your eyes, mouth, or vagina.

Read this Patient Information before you start using fluticasone propionate ointment and each time you get a refill. There may be new information. This information does not take the place of talking to your healthcare provider about your medical condition or your treatment.

What is fluticasone propionate ointment?

Fluticasone propionate ointment is a prescription corticosteroid medicine used on the skin (topical) for the relief of inflammation and itching caused by certain skin conditions in adults.

It is not known if fluticasone propionate ointment is safe and effective in children. Fluticasone propionate ointment is not recommended for use in children.

Before using fluticasone propionate ointment, tell your healthcare provider about all of your medical conditions, including if you:

- have an allergy to any of the ingredients in fluticasone propionate ointment
- have a skin infection at the site to be treated.
  You may also need medicine to treat the skin infection.
- have adrenal gland problems
- have liver problems
- have diabetes
- have thinning skin (atrophy) at the site to be treated
- have cataracts or glaucoma
- are pregnant or plan to become pregnant. It is not known if fluticasone propionate ointment will harm your unborn baby. If you use fluticasone propionate ointment during pregnancy, use fluticasone propionate ointment on the smallest area of the skin and for the shortest time needed.
- are breastfeeding or plan to breastfeed. It is not known if fluticasone propionate ointment can pass into your breast milk and harm your baby. Breastfeeding women should use fluticasone propionate ointment on the smallest area of skin and for the shortest time needed. Do not apply fluticasone propionate ointment directly to the nipple and areola to avoid contact with your baby.

Tell your healthcare provider about all the medicines you take,

including prescription and over-the-counter medicines, vitamins, and herbal supplements. Especially tell your healthcare provider if you take other corticosteroid medicines by mouth or use other products on your skin that contain corticosteroids.

How should I use fluticasone propionate ointment?

- Use fluticasone propionate ointment exactly as your healthcare provider tells you to use it.
- Apply a thin film of fluticasone propionate ointment to the affected area 2 times each day. Gently rub into your skin.
- Do not bandage, cover, or wrap the treated area unless your healthcare provider tells you to.
- Do not use fluticasone propionate ointment on your face, groin, underarms (armpits), unless your healthcare provider tells you to.
- Wash your hands after applying fluticasone propionate ointment, unless your hands are being treated.
- Tell your healthcare provider if your symptoms get worse with fluticasone propionate ointment or if your symptoms do not improve after 2 weeks of treatment.

What are possible side effects of fluticasone propionate ointment?

Fluticasone propionate ointment may cause serious side effects, including:

- Fluticasone propionate ointment can pass through your skin and may cause adrenal gland problems. This is more likely to happen if you use fluticasone propionate ointment for too long, use it over a large treatment area, use it with other topical medicines that contain corticosteroids, cover the treated area, or have liver failure. Your healthcare provider may do blood tests to check your adrenal gland function during and after treatment with fluticasone propionate ointment.
- Skin problems, including skin reactions or thinning of your skin (atrophy), skin infections, and allergic reactions (allergic contact dermatitis) at the treatment site. Tell your healthcare provider if you get any skin reactions such as pain, tenderness, swelling, or healing problems.
- Vision Problems. Topical corticosteroids including fluticasone propionate ointment may increase your chance of developing cataract(s) and glaucoma. Tell your healthcare provider if you develop blurred vision or other vision problems during treatment with fluticasone propionate ointment.

The most common side effects of fluticasone propionate ointment include itching, burning, excessive hair growth, skin redness, hives, and lightheadedness.

These are not all the possible side effects of fluticasone propionate ointment. Call your doctor for medical advice about side effects. You may report side effects to FDA at 1-800-FDA-1088.

How should I store fluticasone propionate ointment?

- Store fluticasone propionate ointment between 20-25°C (68-77°F).

Keep fluticasone propionate ointment and all medicines out of the reach of children.

General information about the safe and effective use of fluticasone propionate ointment.

Medicines are sometimes prescribed for purposes other than those listed in a Patient Information leaflet. Do not use fluticasone propionate ointment for a condition for which it was not prescribed. Do not give fluticasone propionate ointment to other people, even if they have the same symptoms you have. It may harm them. You can ask your pharmacist or healthcare provider for information about fluticasone propionate ointment that is written for health professionals.

What are the ingredients in fluticasone propionate ointment?

Active ingredient: fluticasone propionate

Inactive ingredients: liquid paraffin, microcrystalline wax, propylene glycol, and sorbitan sesquioleate

This Patient Information has been approved by the U.S. Food and Drug Administration.

Manufactured by Padagis®
Yeruham, Israel
www.padagis.com

Rev 11-23

57B00 RC PH2

PACKAGE LABEL

Fluticasone Propionate Ointment 0.005%